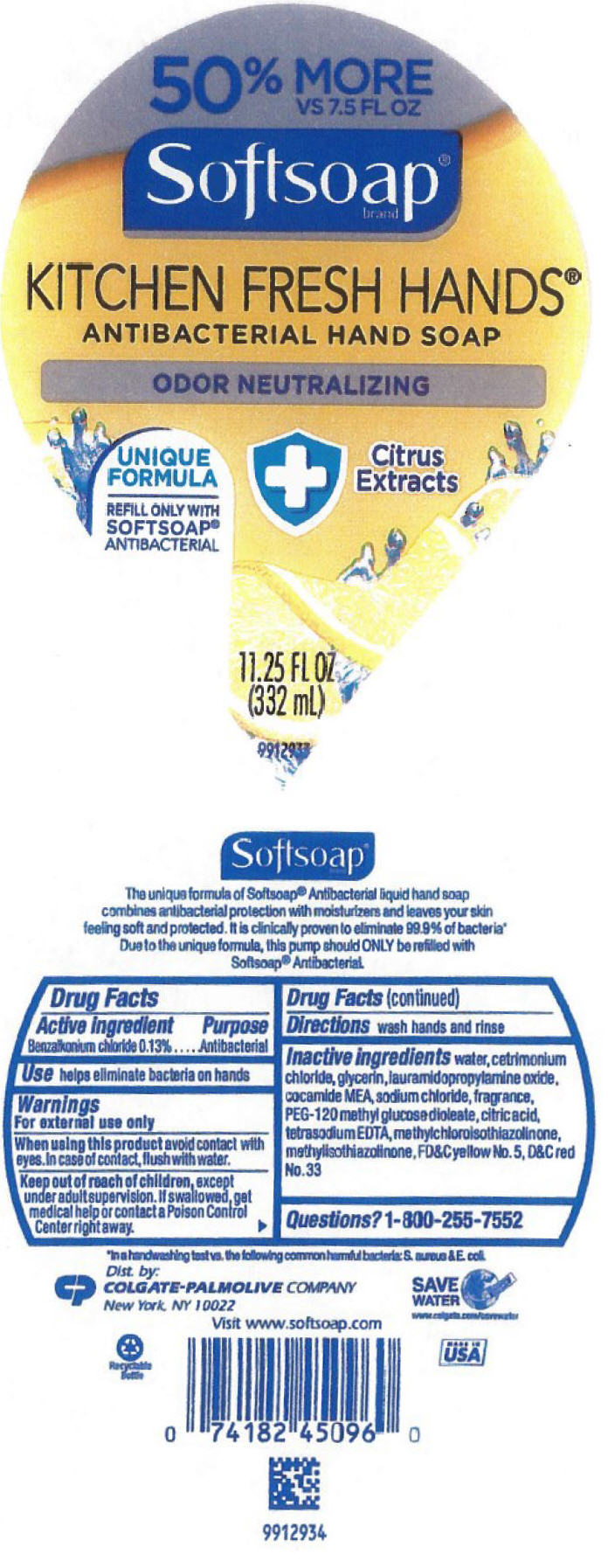 DRUG LABEL: SoftSoap Antibacterial Kitchen Fresh Hands
NDC: 35000-677 | Form: LIQUID
Manufacturer: COLGATE PALMOLIVE COMPANY
Category: otc | Type: HUMAN OTC DRUG LABEL
Date: 20191210

ACTIVE INGREDIENTS: BENZALKONIUM CHLORIDE 1.33 mg/1 mL
INACTIVE INGREDIENTS: WATER; CETRIMONIUM CHLORIDE; GLYCERIN; LAURAMIDOPROPYLAMINE OXIDE; COCO MONOETHANOLAMIDE; SODIUM CHLORIDE; PEG-120 METHYL GLUCOSE DIOLEATE; CITRIC ACID MONOHYDRATE; EDETATE SODIUM; METHYLCHLOROISOTHIAZOLINONE; METHYLISOTHIAZOLINONE; FD&C YELLOW NO. 5; D&C RED NO. 33

SoftSoap® Antibacterial Hand Soap Kitchen Fresh Hands® (11.25 oz)

Drug Facts

Active ingredient

Benzalkonium chloride 0.13%

Purpose

Antibacterial

Use

helps eliminate bacteria on hands

Warnings

For external use only

When using this product avoid contact with eyes. In case of contact, flush with water.

Keep out of reach of children, except under adult supervision. If swallowed, get medical help or contact a Poison Control Center right away.

Directions

wash hands and rinse

Inactive ingredients

water, cetrimonium chloride, glycerin, lauramidopropylamine oxide, cocamide MEA, sodium chloride, fragrance, PEG-120 methyl glucose dioleate, citric acid, tetrasodium EDTA, methylchloroisothiazolinone, methylisothiazolinone, FD&C yellow No. 5, D&C red No. 33

Questions?

1-800-255-7552

Dist. by:
COLGATE-PALMOLIVE COMPANY
New York, NY 10022

PRINCIPAL DISPLAY PANEL - 332 mL Bottle Label

50% MORE
VS 7.5 FL OZ

Softsoap®
brand

KITCHEN FRESH HANDS®
ANTIBACTERIAL HAND SOAP

ODOR NEUTRALIZING

UNIQUE
FORMULA
REFILL ONLY WITH
SOFTSOAP®
ANTIBACTERIAL

Citrus
Extracts

11.25 FL OZ
(332 mL)

9912933